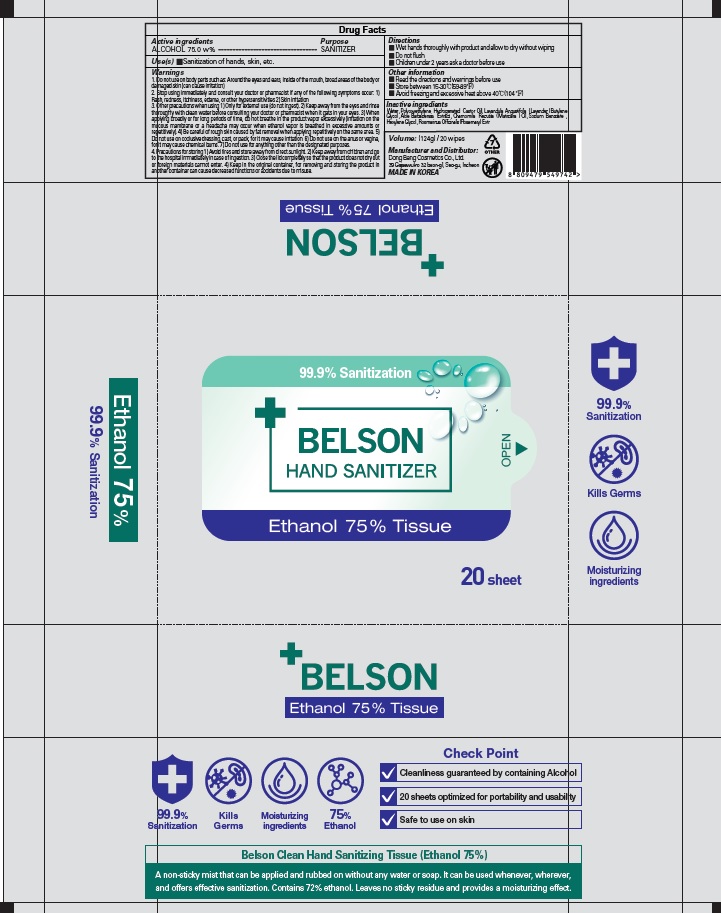 DRUG LABEL: BELSON HAND SANITIZER Ethanol 75 percent Tissue
NDC: 74002-3040 | Form: LIQUID
Manufacturer: DONGBANGCOSMETICS CO.,LTD
Category: otc | Type: HUMAN OTC DRUG LABEL
Date: 20200615

ACTIVE INGREDIENTS: ALCOHOL 75 g/100 g
INACTIVE INGREDIENTS: Water; PEG-60 Hydrogenated Castor Oil; LAVENDER OIL; Butylene Glycol; ALOE VERA LEAF; Sodium Benzoate; Hexylene Glycol; ROSEMARY

ACTIVE INGREDIENT

ALCOHOL 75.0 w%

INACTIVE INGREDIENTS

Water, PEG-60 Hydrogenated Castor Oil, Lavandula Angustifolia (Lavender) Oil, Butylene Glycol, Aloe Barbadensis Extract, Chamomilla Recutita (Matricaria) Oil, Sodium Benzoate, Hexylene Glycol, Rosmarinus Officinalis (Rosemary) Extract

PURPOSE

SANITIZER

WARNINGS

1. Do not use on body parts such as: Around the eyes and ears, inside of the mouth, broad areas of the body or damaged skin (can cause irritation)
2. Stop using immediately and consult your doctor or pharmacist if any of the following symptoms occur: 1) Rash, redness, itchiness, edema, or other hypersensitivities 2) Skin irritation
3. Other precautions when using 1) Only for external use (do not ingest). 2) Keep away from the eyes and rinse thoroughly with clean water before consulting your doctor or pharmacist when it gets in your eyes. 3) When applying broadly or for long periods of time, do not breathe in the product vapor excessively (irritation on the mucous membrane or a headache may occur when ethanol vapor is breathed in excessive amounts or repetitively). 4) Be careful of rough skin caused by fat removal when applying repetitively on the same area. 5) Do not use on occlusive dressing, cast, or pack, for it may cause irritation. 6) Do not use on the anus or vagina, for it may cause chemical burns. 7) Do not use for anything other than the designated purposes.
4. Precautions for storing 1) Avoid fires and store away from direct sunlight. 2) Keep away from children and go to the hospital immediately in case of ingestion. 3) Close the lid completely so that the product does not dry out or foreign materials cannot enter. 4) Keep in the original container, for removing and storing the product in another container can cause decreased functions or accidents due to misuse.

KEEP OUT OF REACH OF CHILDREN

Keep away from children and go to the hospital immediately in case of ingestion.

Uses

Sanitization of hands, skin, etc.

Directions

■ Wet hands thoroughly with product and allow to dry without wiping
■ Do not flush
■ Children under 2 years ask a doctor before use

Other lnformation

■ Read the directions and warnings before use
■ Store between 15-30℃(59-89℉)
■ Avoid freezing and excessive heat above 40℃(104 ℉)